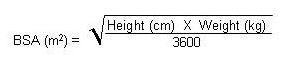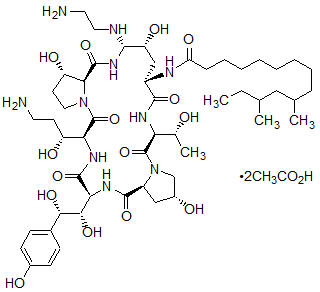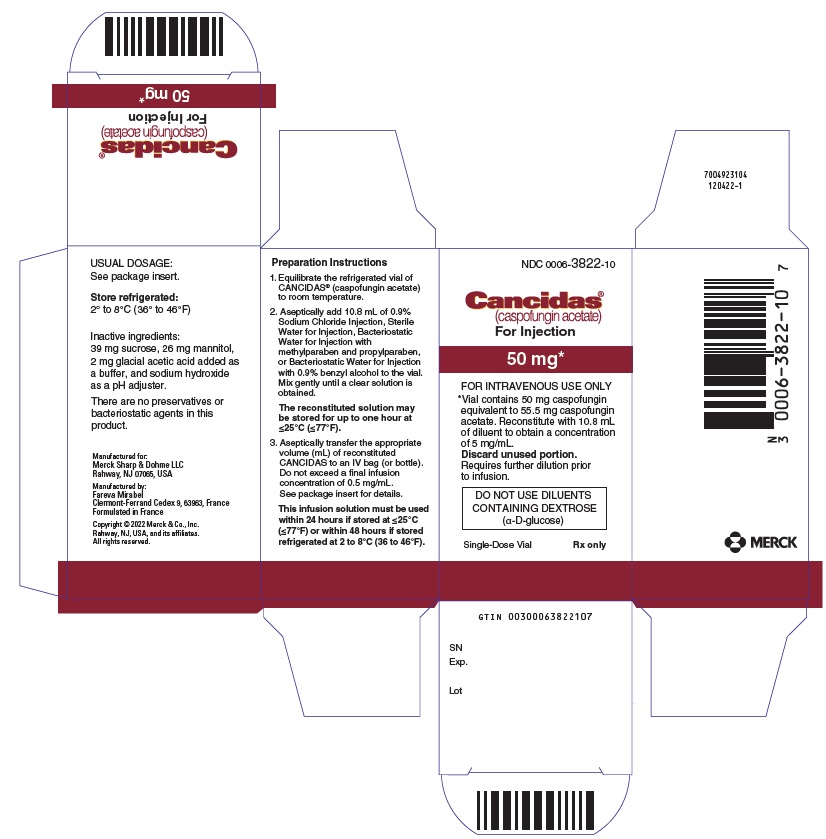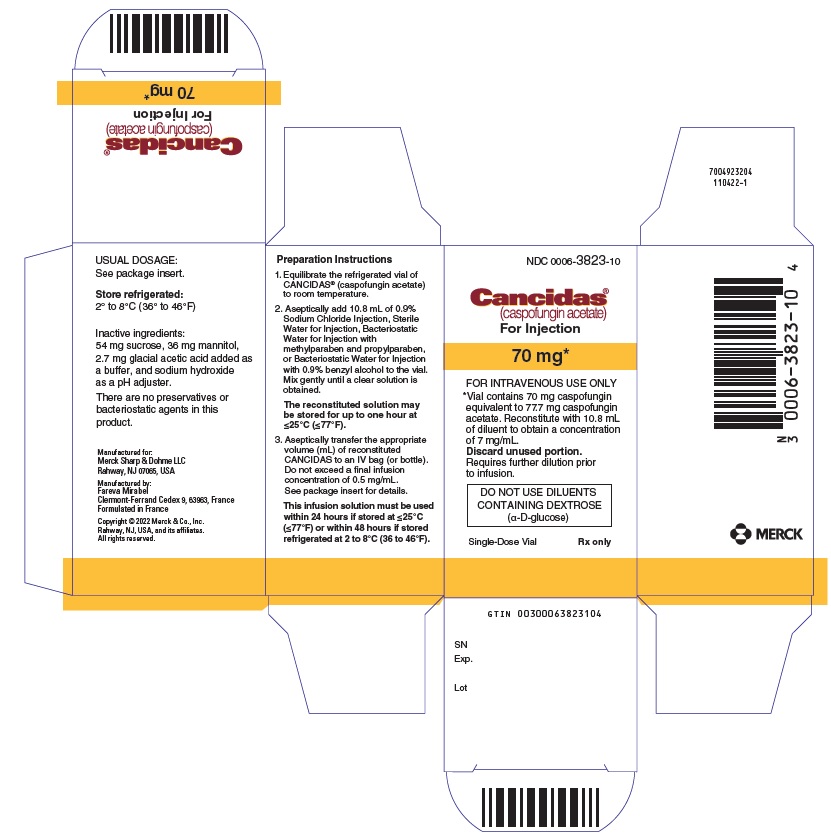 DRUG LABEL: CANCIDAS
NDC: 0006-3822 | Form: INJECTION, POWDER, LYOPHILIZED, FOR SOLUTION
Manufacturer: Merck Sharp & Dohme LLC
Category: prescription | Type: HUMAN PRESCRIPTION DRUG LABEL
Date: 20241011

ACTIVE INGREDIENTS: CASPOFUNGIN ACETATE 5 mg/1 mL
INACTIVE INGREDIENTS: ACETIC ACID; MANNITOL 2.4 mg/1 mL; SODIUM HYDROXIDE; SUCROSE 3.6 mg/1 mL

HIGHLIGHTS OF PRESCRIBING INFORMATION

These highlights do not include all the information needed to use CANCIDAS safely and effectively. See full prescribing information for CANCIDAS.
CANCIDAS® (caspofungin acetate) for injection, for intravenous use
Initial U.S. Approval: 2001

1 INDICATIONS AND USAGE

CANCIDAS is an echinocandin antifungal indicated in adults and pediatric patients (3 months of age and older) for:

- Empirical therapy for presumed fungal infections in febrile, neutropenic patients. (1)
- Treatment of candidemia and the following Candida infections: intra-abdominal abscesses, peritonitis and pleural space infections. (1)
- Treatment of esophageal candidiasis. (1)
- Treatment of invasive aspergillosis in patients who are refractory to or intolerant of other therapies. (1)

2 DOSAGE AND ADMINISTRATION

Important Administration Instructions for All Patients (2.1):

- Administer by slow intravenous (IV) infusion over approximately 1 hour. Do not administer by IV bolus administration.
- Do not mix or co-infuse CANCIDAS with other medications. Do not use diluents containing dextrose (α–D-glucose).

Dosage in Adults [18 years of age and older] (2.2):

- Administer a single 70-mg loading dose on Day 1, followed by 50 mg once daily for all indications except esophageal candidiasis.
- For esophageal candidiasis, use 50 mg once daily with no loading dose.

Dosage in Pediatric Patients [3 months to 17 years of age] (2.3):

- Dosing should be based on the patient's body surface area.
- For all indications, administer a single 70-mg/m^2 loading dose on Day 1, followed by 50 mg/m^2 once daily thereafter.
- Maximum loading dose and daily maintenance dose should not exceed 70 mg, regardless of the patient's calculated dose.

Dosage Adjustments in Patients with Hepatic Impairment (2.4):

Reduce dosage for adult patients with moderate hepatic impairment (35 mg once daily, with a 70 mg loading dose on Day 1 where appropriate).

Dosage Adjustment in Patients Receiving Concomitant Inducers of Hepatic CYP Enzymes (2.5):

- Use 70-mg once daily dose for adult patients on rifampin.
- Consider dose increase to 70 mg once daily for adult patients on nevirapine, efavirenz, carbamazepine, dexamethasone, or phenytoin.
- Pediatric patients receiving these same concomitant medications may also require an increase in dose to 70 mg/m^2 once daily (maximum daily dose not to exceed 70 mg).

3 DOSAGE FORMS AND STRENGTHS

- For Injection: 50 or 70 mg lyophilized powder (plus allowance for overfill) in a single-dose vial for reconstitution (3)

4 CONTRAINDICATIONS

- CANCIDAS is contraindicated in patients with known hypersensitivity to any component of this product. (4)

5 WARNINGS AND PRECAUTIONS

- Hypersensitivity: Anaphylaxis, possible histamine-mediated adverse reactions, including rash, facial swelling, angioedema, pruritus, sensation of warmth or bronchospasm, and cases of Stevens-Johnson syndrome (SJS) and toxic epidermal necrolysis (TEN) have been reported with use of CANCIDAS. Discontinue CANCIDAS at the first sign or symptom of a hypersensitivity reaction and administer appropriate treatment. (5.1)
- Hepatic Effects: Can cause abnormalities in liver enzymes. Isolated cases of hepatic dysfunction, hepatitis, or hepatic failure have been reported. Monitor patients who develop abnormal liver enzymes for evidence of worsening hepatic function, and evaluate risk/benefit of continuing CANCIDAS. (5.2)
- Elevated Liver Enzymes During Concomitant Use with Cyclosporine: Limit use to patients for whom potential benefit outweighs potential risk. Monitor patients who develop abnormal liver function tests (LFTs) during concomitant use with CANCIDAS. (5.3)

6 ADVERSE REACTIONS

- Adults: Most common adverse reactions (incidence 10% or greater) are diarrhea, pyrexia, ALT/AST increased, blood alkaline phosphatase increased, and blood potassium decreased. (6.1)
- Pediatric Patients: Most common adverse reactions (incidence ≥10%) are pyrexia, diarrhea, rash, ALT/AST increased, blood potassium decreased, hypotension, and chills. (6.1)

To report SUSPECTED ADVERSE REACTIONS, contact Merck Sharp & Dohme LLC at 1-877-888-4231 or FDA at 1-800-FDA-1088 or www.fda.gov/medwatch .

8 USE IN SPECIFIC POPULATIONS

- Pregnancy: Based on animal data, may cause fetal harm. (8.1)
- Pediatric Use: Safety and efficacy in neonates and infants less than 3 months old have not been established. (8.4)
- Hepatic Impairment: Reduce dose for adult patients with moderate hepatic impairment (35 mg once daily, with a 70-mg loading dose on Day 1 where appropriate). No data are available in adults with severe impairment or in pediatric patients with any degree of hepatic impairment. (2.4, 8.6, 12.3)

FULL PRESCRIBING INFORMATION

1 INDICATIONS AND USAGE

1.1 Empirical Therapy for Presumed Fungal Infections in Febrile, Neutropenic Patients

CANCIDAS® is indicated as empirical therapy for presumed fungal infections in febrile, neutropenic adult and pediatric patients (3 months of age and older) [see Clinical Studies (14.1, 14.5)].

1.2 Treatment of Candidemia and Other Candida Infections

CANCIDAS is indicated for the treatment of candidemia and the following candida infections: intra-abdominal abscesses, peritonitis, and pleural space infections in adult and pediatric patients (3 months of age and older) [see Clinical Studies (14.2, 14.5)].

Limitations of Use: CANCIDAS has not been studied in endocarditis, osteomyelitis, and meningitis due to Candida.

1.3 Treatment of Esophageal Candidiasis

CANCIDAS is indicated for the treatment of esophageal candidiasis in adult and pediatric patients (3 months of age and older) [see Clinical Studies (14.3, 14.5)].

Limitations of Use: CANCIDAS has not been approved for the treatment of oropharyngeal candidiasis (OPC). In the study that evaluated the efficacy of caspofungin in the treatment of esophageal candidiasis, patients with concomitant OPC had higher relapse rate of the OPC [see Clinical Studies (14.3)].

1.4 Treatment of Invasive Aspergillosis in Patients Who Are Refractory to or Intolerant of Other Therapies

CANCIDAS is indicated for the treatment of invasive aspergillosis in adult and pediatric patients (3 months of age and older) who are refractory to or intolerant of other therapies [see Clinical Studies (14.4, 14.5)].

Limitations of Use: CANCIDAS has not been studied as initial therapy for invasive aspergillosis.

2 DOSAGE AND ADMINISTRATION

2.1 Important Administration Instructions for Use in All Patients

Administer CANCIDAS by slow intravenous (IV) infusion over approximately 1 hour. Do not administer CANCIDAS by IV bolus administration.

2.2 Recommended Dosage in Adult Patients [18 years of age and older]

The dosage and duration of CANCIDAS treatment for each indication are as follows:

Empirical Therapy for Presumed Fungal Infections in Febrile Neutropenic Patients

Administer a single 70-mg loading dose on Day 1, followed by 50 mg once daily thereafter. Duration of treatment should be based on the patient's clinical response. Continue empirical therapy until resolution of neutropenia. In general, treat patients found to have a fungal infection for a minimum of 14 days after the last positive culture and continue treatment for at least 7 days after both neutropenia and clinical symptoms are resolved. If the 50-mg dose is well tolerated but does not provide an adequate clinical response, the daily dose can be increased to 70 mg.

Candidemia and Other Candida Infections

Administer a single 70-mg loading dose on Day 1, followed by 50 mg once daily thereafter. Duration of treatment should be dictated by the patient's clinical and microbiological response. In general, continue antifungal therapy for at least 14 days after the last positive culture. Patients with neutropenia who remain persistently neutropenic may warrant a longer course of therapy pending resolution of the neutropenia.

Esophageal Candidiasis

The dose is 50 mg once daily for 7 to 14 days after symptom resolution. A 70-mg loading dose has not been studied for this indication. Because of the risk of relapse of oropharyngeal candidiasis in patients with HIV infections, suppressive oral therapy could be considered [see Clinical Studies (14.3)].

Invasive Aspergillosis

Administer a single 70-mg loading dose on Day 1, followed by 50 mg once daily thereafter. Duration of treatment should be based upon the severity of the patient's underlying disease, recovery from immunosuppression, and clinical response.

2.3 Recommended Dosing in Pediatric Patients [3 months to 17 years of age]

For all indications, administer a single 70 mg/m^2 loading dose on Day 1, followed by 50 mg/m^2 once daily thereafter. The maximum loading dose and the daily maintenance dose should not exceed 70 mg, regardless of the patient's calculated dose. Dosing in pediatric patients (3 months to 17 years of age) should be based on the patient's body surface area (BSA) as calculated by the Mosteller Formula [see References (15)]:

Following calculation of the patient's BSA, the loading dose in milligrams should be calculated as BSA (m^2) × 70 mg/m^2. The maintenance dose in milligrams should be calculated as BSA (m^2) × 50 mg/m^2.

Duration of treatment should be individualized to the indication, as described for each indication in adults [see Dosage and Administration (2.2)]. If the 50-mg/m^2 daily dose is well tolerated but does not provide an adequate clinical response, the daily dose can be increased to 70 mg/m^2 daily (not to exceed 70 mg).

2.4 Dosage Adjustments in Patients with Hepatic Impairment

Adult patients with mild hepatic impairment (Child-Pugh score 5 to 6) do not need a dosage adjustment. For adult patients with moderate hepatic impairment (Child-Pugh score 7 to 9), CANCIDAS 35 mg once daily is recommended based upon pharmacokinetic data [see Clinical Pharmacology (12.3)] with a 70-mg loading dose administered on Day 1 where appropriate. There is no clinical experience in adult patients with severe hepatic impairment (Child-Pugh score greater than 9) and in pediatric patients with any degree of hepatic impairment.

2.5 Dosage Adjustments in Patients Receiving Concomitant Inducers of Hepatic CYP Enzymes

Adult Patients:

Adult patients on rifampin should receive 70 mg of CANCIDAS once daily. When CANCIDAS is co-administered to adult patients with other inducers of hepatic CYP enzymes such as nevirapine, efavirenz, carbamazepine, dexamethasone, or phenytoin, administration of a daily dose of 70 mg of CANCIDAS should be considered [see Drug Interactions (7)].

Pediatric Patients:

Pediatric patients on rifampin should receive 70 mg/m^2 of CANCIDAS daily (not to exceed an actual daily dose of 70 mg). When CANCIDAS is co-administered to pediatric patients with other inducers of hepatic CYP enzymes, such as efavirenz, nevirapine, phenytoin, dexamethasone, or carbamazepine, a CANCIDAS dose of 70 mg/m^2 once daily (not to exceed 70 mg) should be considered [see Drug Interactions (7)].

2.6 Preparation for Administration

Reconstitution of CANCIDAS for Intravenous Infusion

1. Equilibrate the refrigerated vial of CANCIDAS to room temperature.
2. Aseptically add 10.8 mL of 0.9% Sodium Chloride Injection, Sterile Water for Injection, Bacteriostatic Water for Injection with methylparaben and propylparaben, or Bacteriostatic Water for Injection with 0.9% benzyl alcohol to the vial.
3. Each vial of CANCIDAS contains an intentional overfill of CANCIDAS. Thus, the volume of diluent to be added to each vial and the drug concentration of the resulting solution is listed in Table 1 below.
  Table 1: Information for Preparation of CANCIDAS
  CANCIDAS vial (equivalent to caspofungin) | Volume of diluent to be added [Reconstitution volume of diluent to be added is based on the overfill amount of caspofungin (54.6 mg and 75.6 mg, respectively).] | Resulting Concentration following Reconstitution
  50 mg | 10.8 mL | 5 mg/mL
  70 mg | 10.8 mL | 7 mg/mL
4. The white to off-white cake will dissolve completely. Mix gently until a clear solution is obtained. Visually inspect the reconstituted solution for particulate matter or discoloration during reconstitution and prior to infusion. Do not use if the solution is cloudy or has precipitated.
5. The reconstituted solution of CANCIDAS in the vial may be stored for up to one hour at ≤25°C (≤77°F) prior to the preparation of the infusion solution in the intravenous bag or bottle.
6. CANCIDAS vials are for single-dose only. Discard unused portion.

Dilution of the Reconstituted Solution in the Intravenous Bag for Infusion

1. Aseptically transfer the appropriate volume (mL) of reconstituted CANCIDAS to an intravenous (IV) bag (or bottle) containing 250 mL of 0.9%, 0.45%, or 0.225% Sodium Chloride Injection or Lactated Ringers Injection.
2. Alternatively, the volume (mL) of reconstituted CANCIDAS can be added to a reduced volume of 0.9%, 0.45%, or 0.225% Sodium Chloride Injection or Lactated Ringers Injection, not to exceed a final concentration of 0.5 mg/mL.
3. This diluted infusion solution in the intravenous bag or bottle must be used within 24 hours if stored at ≤25°C (≤77°F) or within 48 hours if stored refrigerated at 2 to 8°C (36 to 46°F).

Important Reconstitution and Dilution Instructions for Pediatric Patients 3 Months of Age and Older

Follow the reconstitution procedures described above using either the 70-mg or 50-mg vial to create the reconstituted solution [see Dosage and Administration (2.3)]. From the reconstituted solution in the vial, remove the volume of drug equal to the calculated loading dose or calculated maintenance dose based on a concentration of 7 mg/mL (if reconstituted from the 70-mg vial) or a concentration of 5 mg/mL (if reconstituted from the 50-mg vial).

The choice of vial should be based on total milligram dose of drug to be administered to the pediatric patient. To help ensure accurate dosing, it is recommended for pediatric doses less than 50 mg that 50-mg vials (with a concentration of 5 mg/mL) be used if available. The 70-mg vial should be reserved for pediatric patients requiring doses greater than 50 mg.

The maximum loading dose and the daily maintenance dose should not exceed 70 mg, regardless of the patient's calculated dose.

2.7 Drug Incompatibilities

Do not mix or co-infuse CANCIDAS with other medications, as there are no data available on the compatibility of CANCIDAS with other intravenous substances, additives, or medications.

Do not use diluents containing dextrose (α-D-glucose), as CANCIDAS is not stable in diluents containing dextrose.

3 DOSAGE FORMS AND STRENGTHS

CANCIDAS 50 mg is a white to off-white lyophilized cake or powder for reconstitution in a single-dose glass vial with a red aluminum band and a plastic cap. CANCIDAS 50-mg vial contains 50 mg of caspofungin equivalent to 55.5 mg of caspofungin acetate.

CANCIDAS 70 mg is a white to off-white lyophilized cake or powder for reconstitution in a single-dose glass vial with a yellow/orange aluminum band and a plastic cap. CANCIDAS 70-mg vial contains 70 mg of caspofungin equivalent to 77.7 mg of caspofungin acetate.

4 CONTRAINDICATIONS

CANCIDAS is contraindicated in patients with known hypersensitivity (e.g., anaphylaxis) to any component of this product [see Adverse Reactions (6)].

5 WARNINGS AND PRECAUTIONS

5.1 Hypersensitivity

Anaphylaxis and other hypersensitivity reactions have been reported during administration of CANCIDAS.

Possible histamine-mediated adverse reactions, including rash, facial swelling, angioedema, pruritus, sensation of warmth or bronchospasm have been reported.

Cases of Stevens-Johnson syndrome (SJS) and toxic epidermal necrolysis (TEN), some with a fatal outcome, have been reported with use of CANCIDAS [see Adverse Reactions (6.2)].

Discontinue CANCIDAS at the first sign or symptom of a hypersensitivity reaction and administer appropriate treatment.

5.2 Hepatic Effects

Laboratory abnormalities in liver function tests have been seen in healthy volunteers and in adult and pediatric patients treated with CANCIDAS. In some adult and pediatric patients with serious underlying conditions who were receiving multiple concomitant medications with CANCIDAS, isolated cases of clinically significant hepatic dysfunction, hepatitis, and hepatic failure have been reported; a causal relationship to CANCIDAS has not been established. Monitor patients who develop abnormal liver function tests during CANCIDAS therapy for evidence of worsening hepatic function and evaluated for risk/benefit of continuing CANCIDAS therapy.

5.3 Elevated Liver Enzymes During Concomitant Use With Cyclosporine

Elevated liver enzymes have occurred in patients receiving CANCIDAS and cyclosporine concomitantly. Only use CANCIDAS and cyclosporine in those patients for whom the potential benefit outweighs the potential risk. Patients who develop abnormal liver enzymes during concomitant therapy should be monitored and the risk/benefit of continuing therapy should be evaluated.

6 ADVERSE REACTIONS

The following serious adverse reactions are discussed in detail in another section of the labeling:

- Hypersensitivity [see Warnings and Precautions (5.1)]
- Hepatic Effects [see Warnings and Precautions (5.2)]
- Elevated Liver Enzymes During Concomitant Use With Cyclosporine [see Warnings and Precautions (5.3)]

6.1 Clinical Trials Experience

Because clinical trials are conducted under widely varying conditions, adverse reaction rates observed in clinical trials of CANCIDAS cannot be directly compared to rates in clinical trials of another drug and may not reflect the rates observed in practice.

Clinical Trials Experience in Adults

The overall safety of CANCIDAS was assessed in 1865 adult individuals who received single or multiple doses of CANCIDAS: 564 febrile, neutropenic patients (empirical therapy study); 382 patients with candidemia and/or intra-abdominal abscesses, peritonitis, or pleural space infections (including 4 patients with chronic disseminated candidiasis); 297 patients with esophageal and/or oropharyngeal candidiasis; 228 patients with invasive aspergillosis; and 394 individuals in phase I studies. In the empirical therapy study patients had undergone hematopoietic stem-cell transplantation or chemotherapy. In the studies involving patients with documented Candida infections, the majority of the patients had serious underlying medical conditions (e.g., hematologic or other malignancy, recent major surgery, HIV) requiring multiple concomitant medications. Patients in the noncomparative Aspergillus studies often had serious predisposing medical conditions (e.g., bone marrow or peripheral stem cell transplants, hematologic malignancy, solid tumors or organ transplants) requiring multiple concomitant medications.

Empirical Therapy for Presumed Fungal Infections in Febrile Neutropenic Patients

In the randomized, double-blinded empirical therapy study, patients received either CANCIDAS 50 mg/day (following a 70-mg loading dose) or AmBisome® (amphotericin B liposome for injection, 3 mg/kg/day). In this study clinical or laboratory hepatic adverse reactions were reported in 39% and 45% of patients in the CANCIDAS and AmBisome groups, respectively. Also reported was an isolated, serious adverse reaction of hyperbilirubinemia. Adverse reactions occurring in 7.5% or greater of the patients in either treatment group are presented in Table 2.

Table 2: Adverse Reactions Among Patients with Persistent Fever and Neutropenia Incidence 7.5% or greater for at Least One Treatment Group
Adverse Reactions | CANCIDAS [70 mg on Day 1, then 50 mg once daily for the remainder of treatment; daily dose was increased to 70 mg for 73 patients.] N=564 (percent) | AmBisome [3 mg/kg/day; daily dose was increased to 5 mg/kg for 74 patients.] N=547 (percent)
All Systems, Any Adverse Reaction | 95 | 97
Investigations | 58 | 63
Alanine Aminotransferase Increased | 18 | 20
Blood Alkaline Phosphatase Increased | 15 | 23
Blood Potassium Decreased | 15 | 23
Aspartate Aminotransferase Increased | 14 | 17
Blood Bilirubin Increased | 10 | 14
Blood Magnesium Decreased | 7 | 9
Blood Glucose Increased | 6 | 9
Bilirubin Conjugated Increased | 5 | 9
Blood Urea Increased | 4 | 8
Blood Creatinine Increased | 3 | 11
General Disorders and Administration Site Conditions | 57 | 63
Pyrexia | 27 | 29
Chills | 23 | 31
Edema Peripheral | 11 | 12
Mucosal Inflammation | 6 | 8
Gastrointestinal Disorders | 50 | 55
Diarrhea | 20 | 16
Nausea | 11 | 20
Abdominal Pain | 9 | 11
Vomiting | 9 | 17
Respiratory, Thoracic and Mediastinal Disorders | 47 | 49
Dyspnea | 9 | 10
Skin and Subcutaneous Tissue Disorders | 42 | 37
Rash | 16 | 14
Nervous System Disorders | 25 | 27
Headache | 11 | 12
Metabolism and Nutrition Disorders | 21 | 24
Hypokalemia | 6 | 8
Vascular Disorders | 20 | 23
Hypotension | 6 | 10
Cardiac Disorders | 16 | 19
Tachycardia | 7 | 9
Within any system organ class, individuals may experience more than 1 adverse reaction.

The proportion of patients who experienced an infusion-related adverse reaction (defined as a systemic event, such as pyrexia, chills, flushing, hypotension, hypertension, tachycardia, dyspnea, tachypnea, rash, or anaphylaxis, that developed during the study therapy infusion and one hour following infusion) was significantly lower in the group treated with CANCIDAS (35%) than in the group treated with AmBisome (52%).

To evaluate the effect of CANCIDAS and AmBisome on renal function, nephrotoxicity was defined as doubling of serum creatinine relative to baseline or an increase of greater than or equal to 1 mg/dL in serum creatinine if baseline serum creatinine was above the upper limit of the normal range. Among patients whose baseline creatinine clearance was greater than 30 mL/min, the incidence of nephrotoxicity was significantly lower in the group treated with CANCIDAS (3%) than in the group treated with AmBisome (12%).

Candidemia and Other Candida Infections

In the randomized, double-blinded invasive candidiasis study, patients received either CANCIDAS 50 mg/day (following a 70-mg loading dose) or amphotericin B 0.6 to 1 mg/kg/day. Adverse reactions occurring in 10% or greater of the patients in either treatment group are presented in Table 3.

Table 3: Adverse Reactions Among Patients with Candidemia or Other Candida Infections [Intra-abdominal abscesses, peritonitis and pleural space infections.] Incidence 10% or Greater for at Least One Treatment Group
Adverse Reactions | CANCIDAS 50 mg [Patients received CANCIDAS 70 mg on Day 1, then 50 mg once daily for the remainder of their treatment.] N=114 (percent) | Amphotericin B N=125 (percent)
All Systems, Any Adverse Reaction | 96 | 99
Investigations | 67 | 82
Blood Potassium Decreased | 23 | 32
Blood Alkaline Phosphatase Increased | 21 | 32
Hemoglobin Decreased | 18 | 23
Alanine Aminotransferase Increased | 16 | 15
Aspartate Aminotransferase Increased | 16 | 14
Blood Bilirubin Increased | 13 | 17
Hematocrit Decreased | 13 | 18
Blood Creatinine Increased | 11 | 28
Red Blood Cells Urine Positive | 10 | 10
Blood Urea Increased | 9 | 23
Bilirubin Conjugated Increased | 8 | 14
Gastrointestinal Disorders | 49 | 53
Vomiting | 17 | 16
Diarrhea | 14 | 10
Nausea | 9 | 17
General Disorders and Administration Site Conditions | 47 | 63
Pyrexia | 13 | 33
Edema Peripheral | 11 | 12
Chills | 9 | 30
Respiratory, Thoracic and Mediastinal Disorders | 40 | 54
Tachypnea | 1 | 11
Cardiac Disorders | 26 | 34
Tachycardia | 8 | 12
Skin and Subcutaneous Tissue Disorders | 25 | 28
Rash | 4 | 10
Vascular Disorders | 25 | 38
Hypotension | 10 | 16
Blood and Lymphatic System Disorders | 15 | 13
Anemia | 11 | 9
Within any system organ class, individuals may experience more than 1 adverse reaction.

The proportion of patients who experienced an infusion-related adverse reaction (defined as a systemic event, such as pyrexia, chills, flushing, hypotension, hypertension, tachycardia, dyspnea, tachypnea, rash, or anaphylaxis, that developed during the study therapy infusion and one hour following infusion) was significantly lower in the group treated with CANCIDAS (20%) than in the group treated with amphotericin B (49%).

To evaluate the effect of CANCIDAS and amphotericin B on renal function, nephrotoxicity was defined as doubling of serum creatinine relative to baseline or an increase of greater than or equal to 1 mg/dL in serum creatinine if baseline serum creatinine was above the upper limit of the normal range. In a subgroup of patients whose baseline creatinine clearance was greater than 30 mL/min, the incidence of nephrotoxicity was significantly lower in the group treated with CANCIDAS than in the group treated with amphotericin B.

In a second randomized, double-blinded invasive candidiasis study, patients received either CANCIDAS 50 mg/day (following a 70-mg loading dose) or CANCIDAS 150 mg/day. The proportion of patients who experienced any adverse reaction was similar in the 2 treatment groups; however, this study was not large enough to detect differences in rare or unexpected adverse reactions. Adverse reactions occurring in 5% or greater of the patients in either treatment group are presented in Table 4.

Table 4: Adverse Reactions Among Patients with Candidemia or other Candida Infections [Intra-abdominal abscesses, peritonitis and pleural space infections.] Incidence 5% or Greater for at Least One Treatment Group
Adverse Reactions | CANCIDAS 50 mg [Patients received CANCIDAS 70 mg on Day 1, then 50 mg once daily for the remainder of their treatment.] N=104 (percent) | CANCIDAS 150 mg N=100 (percent)
All Systems, Any Adverse Reaction | 83 | 83
General Disorders and Administration Site Conditions | 33 | 27
Pyrexia | 6 | 6
Gastrointestinal Disorders | 30 | 33
Vomiting | 11 | 6
Diarrhea | 6 | 7
Nausea | 5 | 7
Investigations | 28 | 35
Alkaline Phosphatase Increased | 12 | 9
Aspartate Aminotransferase Increased | 6 | 9
Blood potassium decreased | 6 | 8
Alanine Aminotransferase Increased | 4 | 7
Vascular Disorders | 19 | 18
Hypotension | 7 | 3
Hypertension | 5 | 6
Within any system organ class, individuals may experience more than 1 adverse event

Esophageal Candidiasis and Oropharyngeal Candidiasis

Adverse reactions occurring in 10% or greater of patients with esophageal and/or oropharyngeal candidiasis are presented in Table 5.

Table 5: Adverse Reactions Among Patients with Esophageal and/or Oropharyngeal Candidiasis Incidence 10% or Greater for at Least One Treatment Group
Adverse Reactions | CANCIDAS 50 mg [Derived from a comparator-controlled clinical study.] N=83 (percent) | Fluconazole IV 200 mg N=94 (percent)
All Systems, Any Adverse Reaction | 90 | 93
Gastrointestinal Disorders | 58 | 50
Diarrhea | 27 | 18
Nausea | 15 | 15
Investigations | 53 | 61
Hemoglobin Decreased | 21 | 16
Hematocrit Decreased | 18 | 16
Aspartate Aminotransferase Increased | 13 | 19
Blood Alkaline Phosphatase Increased | 13 | 17
Alanine Aminotransferase Increased | 12 | 17
White Blood Cell Count Decreased | 12 | 19
General Disorders and Administration Site Conditions | 31 | 36
Pyrexia | 21 | 21
Vascular Disorders | 19 | 15
Phlebitis | 18 | 11
Nervous System Disorders | 18 | 17
Headache | 15 | 9
Within any system organ class, individuals may experience more than 1 adverse reaction.

Invasive Aspergillosis

In an open-label, noncomparative aspergillosis study, in which 69 patients received CANCIDAS (70-mg loading dose on Day 1 followed by 50 mg daily), the following adverse reactions were observed with an incidence of 12.5% or greater: blood alkaline phosphatase increased (22%), hypotension (20%), respiratory failure (20%), pyrexia (17%), diarrhea (15%), nausea (15%), headache (15%), rash (13%), alanine aminotransferase increased (13%), aspartate aminotransferase increased (13%), blood bilirubin increased (13%), and blood potassium decreased (13%). Also reported in this patient population were pulmonary edema, ARDS (adult respiratory distress syndrome), and radiographic infiltrates.

Clinical Trials Experience in Pediatric Patients (3 months to 17 years of age)

The overall safety of CANCIDAS was assessed in 171 pediatric patients who received single or multiple doses of CANCIDAS. The distribution among the 153 pediatric patients who were over the age of 3 months was as follows: 104 febrile, neutropenic patients; 38 patients with candidemia and/or intra-abdominal abscesses, peritonitis, or pleural space infections; 1 patient with esophageal candidiasis; and 10 patients with invasive aspergillosis. The overall safety profile of CANCIDAS in pediatric patients is comparable to that in adult patients. Table 6 shows the incidence of adverse reactions reported in 7.5% or greater of pediatric patients in clinical studies.

One patient (0.6%) receiving CANCIDAS, and three patients (12%) receiving AmBisome developed a serious drug-related adverse reaction. Two patients (1%) were discontinued from CANCIDAS and three patients (12%) were discontinued from AmBisome due to a drug-related adverse reaction. The proportion of patients who experienced an infusion-related adverse reaction (defined as a systemic event, such as pyrexia, chills, flushing, hypotension, hypertension, tachycardia, dyspnea, tachypnea, rash, or anaphylaxis, that developed during the study therapy infusion and one hour following infusion) was 22% in the group treated with CANCIDAS and 35% in the group treated with AmBisome.

Table 6: Adverse Reactions Among Pediatric Patients (0 months to 17 years of age) Incidence 7.5% or Greater for at Least One Treatment Group
 | Noncomparative Clinical Studies | Comparator-Controlled Clinical Study of Empirical Therapy
Adverse Reactions | CANCIDAS Any Dose N=115 (percent) | CANCIDAS 50 mg/m^2 [70 mg/m^2 on Day 1, then 50 mg/m^2 once daily for the remainder of the treatment.] N=56 (percent) | AmBisome 3 mg/kg N=26 (percent)
All Systems, Any Adverse Reaction | 95 | 96 | 89
Investigations | 55 | 41 | 50
Blood Potassium Decreased | 18 | 9 | 27
Aspartate Aminotransferase Increased | 17 | 2 | 12
Alanine Aminotransferase Increased | 14 | 5 | 12
Blood Potassium Increased | 3 | 0 | 8
General Disorders and Administration Site Conditions | 47 | 59 | 42
Pyrexia | 29 | 30 | 23
Chills | 10 | 13 | 8
Mucosal Inflammation | 10 | 4 | 4
Edema | 3 | 4 | 8
Gastrointestinal Disorders | 42 | 41 | 35
Diarrhea | 17 | 7 | 15
Vomiting | 8 | 11 | 12
Abdominal Pain | 7 | 4 | 12
Nausea | 4 | 4 | 8
Infections and Infestations | 40 | 30 | 35
Central Line Infection | 1 | 9 | 0
Skin and Subcutaneous Tissue Disorders | 33 | 41 | 39
Pruritus | 7 | 6 | 8
Rash | 6 | 23 | 8
Erythema | 4 | 9 | 0
Vascular Disorders | 24 | 21 | 19
Hypotension | 12 | 9 | 8
Hypertension | 10 | 9 | 4
Metabolism and Nutrition Disorders | 22 | 11 | 23
Hypokalemia | 8 | 5 | 4
Cardiac Disorders | 17 | 13 | 19
Tachycardia | 4 | 11 | 19
Nervous System Disorders | 13 | 16 | 8
Headache | 5 | 9 | 4
Musculoskeletal and Connective Tissue Disorders | 11 | 14 | 12
Back Pain | 4 | 0 | 8
Blood and Lymphatic System Disorders | 10 | 2 | 15
Anemia | 2 | 0 | 8
Within any system organ class, individuals may experience more than 1 adverse reaction.

Overall Safety Experience of CANCIDAS in Clinical Trials

The overall safety of CANCIDAS was assessed in 2036 individuals (including 1642 adult or pediatric patients and 394 volunteers) from 34 clinical studies. These individuals received single or multiple (once daily) doses of CANCIDAS, ranging from 5 mg to 210 mg. Full safety data is available from 1951 individuals, as the safety data from 85 patients enrolled in 2 compassionate use studies was limited solely to serious adverse reactions. Adverse reactions which occurred in 5% or greater of all individuals who received CANCIDAS in these trials are shown in Table 7.

Overall, 1665 of the 1951 (85%) patients/volunteers who received CANCIDAS experienced an adverse reaction.

Table 7: Adverse Reactions [Defined as an adverse reaction, regardless of causality, while on CANCIDAS or during the 14-day post-CANCIDAS follow-up period.] in Patients Who Received CANCIDAS in Clinical Trials [Incidence for each preferred term is 5% or greater among individuals who received at least 1 dose of CANCIDAS.] Incidence 5% or Greater for at Least One Treatment Group
Adverse Reactions [Within any system organ class, individuals may experience more than 1 adverse event.] | CANCIDAS (N = 1951)
 | n | (%)
All Systems, Any Adverse Reaction | 1665 | (85)
Investigations | 901 | (46)
Alanine Aminotransferase Increased | 258 | (13)
Aspartate Aminotransferase Increased | 233 | (12)
Blood Alkaline Phosphatase Increased | 232 | (12)
Blood Potassium Decreased | 220 | (11)
Blood Bilirubin Increased | 117 | (6)
General Disorders and Administration Site Conditions | 843 | (43)
Pyrexia | 381 | (20)
Chills | 192 | (10)
Edema Peripheral | 110 | (6)
Gastrointestinal Disorders | 754 | (39)
Diarrhea | 273 | (14)
Nausea | 166 | (9)
Vomiting | 146 | (8)
Abdominal Pain | 112 | (6)
Infections and Infestations | 730 | (37)
Pneumonia | 115 | (6)
Respiratory, Thoracic, and Mediastinal Disorders | 613 | (31)
Cough | 111 | (6)
Skin and Subcutaneous Tissue Disorders | 520 | (27)
Rash | 159 | (8)
Erythema | 98 | (5)
Nervous System Disorders | 412 | (21)
Headache | 193 | (10)
Vascular Disorders | 344 | (18)
Hypotension | 118 | (6)

Clinically significant adverse reactions, regardless of causality or incidence which occurred in less than 5% of patients are listed below.

- Blood and lymphatic system disorders: anemia, coagulopathy, febrile neutropenia, neutropenia, thrombocytopenia
- Cardiac disorders: arrhythmia, atrial fibrillation, bradycardia, cardiac arrest, myocardial infarction, tachycardia
- Gastrointestinal disorders: abdominal distension, abdominal pain upper, constipation, dyspepsia
- General disorders and administration site conditions: asthenia, fatigue, infusion site pain/pruritus/swelling, mucosal inflammation, edema
- Hepatobiliary disorders: hepatic failure, hepatomegaly, hepatotoxicity, hyperbilirubinemia, jaundice
- Infections and infestations: bacteremia, sepsis, urinary tract infection
- Metabolic and nutrition disorders: anorexia, decreased appetite, fluid overload, hypomagnesemia, hypercalcemia, hyperglycemia, hypokalemia
- Musculoskeletal, connective tissue, and bone disorders: arthralgia, back pain, pain in extremity
- Nervous system disorders: convulsion, dizziness, somnolence, tremor
- Psychiatric disorders: anxiety, confusional state, depression, insomnia
- Renal and urinary disorders: hematuria, renal failure
- Respiratory, thoracic, and mediastinal disorders: dyspnea, epistaxis, hypoxia, tachypnea
- Skin and subcutaneous tissue disorders: erythema, petechiae, skin lesion, urticaria
- Vascular disorders: flushing, hypertension, phlebitis

6.2 Postmarketing Experience

The following additional adverse reactions have been identified during the post-approval use of CANCIDAS. Because these reactions are reported voluntarily from a population of uncertain size, it is not always possible to reliably estimate their frequency or establish a causal relationship to drug exposure.

- Gastrointestinal disorders: pancreatitis
- Hepatobiliary disorders: hepatic necrosis
- Skin and subcutaneous tissue disorders: erythema multiforme, toxic epidermal necrolysis, Stevens-Johnson syndrome, and skin exfoliation
- Renal and urinary disorders: clinically significant renal dysfunction
- General disorders and administration site conditions: swelling and peripheral edema
- Laboratory abnormalities: gamma-glutamyltransferase increased

7 DRUG INTERACTIONS

Cyclosporine: In two adult clinical studies, cyclosporine (one 4 mg/kg dose or two 3 mg/kg doses) increased the AUC of CANCIDAS. CANCIDAS did not increase the plasma levels of cyclosporine. There were transient increases in liver ALT and AST when CANCIDAS and cyclosporine were co-administered. Monitor patients who develop abnormal liver enzymes during concomitant therapy and evaluate the risk/benefit of continuing therapy [see Warnings and Precautions (5.2) and Clinical Pharmacology (12.3)].

Tacrolimus: For patients receiving CANCIDAS and tacrolimus, standard monitoring of tacrolimus trough whole blood concentrations and appropriate tacrolimus dosage adjustments are recommended.

Inducers of Hepatic CYP Enzymes

Rifampin: Rifampin is a potent CYP3A4 inducer and concomitant administration with CANCIDAS is expected to reduce the plasma concentrations of CANCIDAS. Therefore, adult patients on rifampin should receive 70 mg of CANCIDAS daily and pediatric patients on rifampin should receive 70 mg/m^2 of CANCIDAS daily (not to exceed an actual daily dose of 70 mg) [see Dosage and Administration (2.5) and Clinical Pharmacology (12.3)].

Other Inducers of Hepatic CYP Enzymes

Adults: When CANCIDAS is co-administered to adult patients with other inducers of hepatic CYP enzymes, such as efavirenz, nevirapine, phenytoin, dexamethasone, or carbamazepine, administration of a daily dose of 70 mg of CANCIDAS should be considered [see Dosage and Administration (2.5) and Clinical Pharmacology (12.3)].

Pediatric Patients: When CANCIDAS is co-administered to pediatric patients with other inducers of hepatic CYP enzymes, such as efavirenz, nevirapine, phenytoin, dexamethasone, or carbamazepine, administration of a daily dose of 70 mg/m^2 CANCIDAS (not to exceed an actual daily dose of 70 mg) should be considered [see Dosage and Administration (2.5) and Clinical Pharmacology (12.3)].

8 USE IN SPECIFIC POPULATIONS

8.1 Pregnancy

Risk Summary

Based on animal data, CANCIDAS may cause fetal harm (see Data). There are insufficient human data to establish whether there is a drug-associated risk for major birth defects, miscarriage, or adverse maternal or fetal outcomes with CANCIDAS use in pregnant women.

In animal studies, caspofungin caused embryofetal toxicity, including increased resorptions, increased peri-implantation loss, and incomplete ossification at multiple fetal sites when administered intravenously to pregnant rats and rabbits during organogenesis at doses up to 0.8 and 2 times the clinical dose, respectively (see Data). Advise patients of the potential risk to the fetus.

The estimated background risk of major birth defects and miscarriage for the indicated population is unknown. All pregnancies have a background risk of birth defect, loss, or other adverse outcomes. In the U.S. general population, the estimated background risk of major birth defects and miscarriage in clinically recognized pregnancies is 2 to 4% and 15 to 20%, respectively.

Data

Animal Data

In animal reproduction studies, pregnant rats dosed intravenously with caspofungin during organogenesis (gestational days [GD] 6 to 20) at 0.5, 2, or 5 mg/kg/day (up to 0.8 times the clinical dose based on body surface area comparison) showed increased resorptions and peri-implantation losses at 5 mg/kg/day. Incomplete ossification of the skull and torso and increased incidences of cervical rib were noted in offspring born to pregnant rats treated at doses up to 5 mg/kg/day. In pregnant rabbits treated with intravenous caspofungin during organogenesis (GD 7 to 20) at doses of 1, 3, or 6 mg/kg/day (approximately 2 times the clinical dose based on body surface area comparison), increased fetal resorptions and increased incidence of incomplete ossification of the talus/calcaneus in offspring were observed at the highest dose tested. Caspofungin crossed the placenta in rats and rabbits and was detectable in fetal plasma.

In peri- and postnatal development study in rats, intravenous caspofungin administered at 0.5, 2 or 5 mg/kg/day from Day 6 of gestation through Day 20 of lactation was not associated with any adverse effects on reproductive performance or subsequent development of first generation (F1) offspring or malformations in second generation (F2) offspring.

8.2 Lactation

Risk Summary

There are no data on the presence of caspofungin in human milk, the effects on the breast-fed child, or the effects on milk production. Caspofungin was found in the milk of lactating, drug-treated rats.

The developmental and health benefits of breastfeeding should be considered along with the mother's clinical need for CANCIDAS and any potential adverse effects on the breastfed child from CANCIDAS or from the underlying maternal condition.

8.4 Pediatric Use

The safety and effectiveness of CANCIDAS in pediatric patients 3 months to 17 years of age are supported by evidence from adequate and well-controlled studies in adults, pharmacokinetic data in pediatric patients, and additional data from prospective studies in pediatric patients 3 months to 17 years of age for the following indications [see Indications and Usage (1)]:

- Empirical therapy for presumed fungal infections in febrile, neutropenic patients.
- Treatment of candidemia and the following Candida infections: intra-abdominal abscesses, peritonitis, and pleural space infections.
- Treatment of esophageal candidiasis.
- Treatment of invasive aspergillosis in patients who are refractory to or intolerant of other therapies (e.g., amphotericin B, lipid formulations of amphotericin B, itraconazole).

The efficacy and safety of CANCIDAS has not been adequately studied in prospective clinical trials involving neonates and infants under 3 months of age. Although limited pharmacokinetic data were collected in neonates and infants below 3 months of age, these data are insufficient to establish a safe and effective dose of caspofungin in the treatment of neonatal candidiasis. Invasive candidiasis in neonates has a higher rate of CNS and multi-organ involvement than in older patients; the ability of CANCIDAS to penetrate the blood-brain barrier and to treat patients with meningitis and endocarditis is unknown.

CANCIDAS has not been studied in pediatric patients with endocarditis, osteomyelitis, and meningitis due to Candida. CANCIDAS has also not been studied as initial therapy for invasive aspergillosis in pediatric patients.

In clinical trials, 171 pediatric patients (0 months to 17 years of age), including 18 patients who were less than 3 months of age, were given intravenous CANCIDAS. Pharmacokinetic studies enrolled a total of 66 pediatric patients, and an additional 105 pediatric patients received CANCIDAS in safety and efficacy studies [see Clinical Pharmacology (12.3) and Clinical Studies (14.5)]. The majority of the pediatric patients received CANCIDAS at a once-daily maintenance dose of 50 mg/m^2 for a mean duration of 12 days (median 9, range 1-87 days). In all studies, safety was assessed by the investigator throughout study therapy and for 14 days following cessation of study therapy. The most common adverse reactions in pediatric patients treated with CANCIDAS were pyrexia (29%), blood potassium decreased (15%), diarrhea (14%), increased aspartate aminotransferase (12%), rash (12%), increased alanine aminotransferase (11%), hypotension (11%), and chills (11%) [see Adverse Reactions (6.2)].

Postmarketing hepatobiliary adverse reactions have been reported in pediatric patients with serious underlying medical conditions [see Warnings and Precautions (5.3)].

8.5 Geriatric Use

Clinical studies of CANCIDAS did not include sufficient numbers of patients aged 65 and over to determine whether they respond differently from younger patients. Although the number of elderly patients was not large enough for a statistical analysis, no overall differences in safety or efficacy were observed between these and younger patients. Plasma concentrations of caspofungin in healthy older men and women (65 years of age and older) were increased slightly (approximately 28% in AUC) compared to young healthy men. A similar effect of age on pharmacokinetics was seen in patients with candidemia or other Candida infections (intra-abdominal abscesses, peritonitis, or pleural space infections). No dose adjustment is recommended for the elderly; however, greater sensitivity of some older individuals cannot be ruled out.

8.6 Patients with Hepatic Impairment

Adult patients with mild hepatic impairment (Child-Pugh score 5 to 6) do not need a dosage adjustment. For adult patients with moderate hepatic impairment (Child-Pugh score 7 to 9), CANCIDAS 35 mg once daily is recommended based upon pharmacokinetic data [see Clinical Pharmacology (12.3)]. However, where recommended, a 70-mg loading dose should still be administered on Day 1 [see Dosage and Administration (2.4) and Clinical Pharmacology (12.3)]. There is no clinical experience in adult patients with severe hepatic impairment (Child-Pugh score greater than 9) and in pediatric patients 3 months to 17 years of age with any degree of hepatic impairment.

8.7 Patients with Renal Impairment

No dosage adjustment is necessary for patients with renal impairment. Caspofungin is not dialyzable; thus, supplementary dosing is not required following hemodialysis [see Clinical Pharmacology (12.3)].

10 OVERDOSAGE

In 6 healthy subjects who received a single 210-mg dose, no significant adverse reactions were reported. Multiple doses above 150 mg daily have not been studied. Caspofungin is not dialyzable.

In clinical trials, one pediatric patient (16 years of age) unintentionally received a single dose of caspofungin of 113 mg (on Day 1), followed by 80 mg daily for an additional 7 days. No clinically significant adverse reactions were reported.

11 DESCRIPTION

CANCIDAS is a sterile, lyophilized product for intravenous (IV) infusion that contains a semisynthetic lipopeptide (echinocandin) compound synthesized from a fermentation product of Glarea lozoyensis. CANCIDAS is an echinocandin antifungal that inhibits the synthesis of β (1,3)-D-glucan, an integral component of the fungal cell wall.

CANCIDAS (caspofungin acetate) is 1-[(4R,5S)-5-[(2-aminoethyl)amino]-N^2-(10,12-dimethyl-1-oxotetradecyl)-4-hydroxy-L-ornithine]-5-[(3R)-3-hydroxy-L-ornithine] pneumocandin B0 diacetate (salt). CANCIDAS 50 mg contains 50 mg of caspofungin equivalent to 55.5 mg of caspofungin acetate. CANCIDAS 50 mg also contains: 39 mg sucrose, 26 mg mannitol, 2 mg glacial acetic acid added as a buffering agent, and sodium hydroxide added as a pH adjuster ingredient. CANCIDAS 70 mg contains 70 mg of caspofungin equivalent to 77.7 mg of caspofungin acetate. CANCIDAS 70 mg also contains 54 mg sucrose, 36 mg mannitol, 2.7 mg glacial acetic acid added as a buffering agent, and sodium hydroxide added as a pH adjuster ingredient.

Caspofungin acetate is a hygroscopic, white to off-white powder. It is freely soluble in water and methanol, and slightly soluble in ethanol. The pH of a saturated aqueous solution of caspofungin acetate is approximately 6.6. The empirical formula is C52H88N10O15∙2C2H4O2 and the formula weight is 1213.42. The structural formula is:

12 CLINICAL PHARMACOLOGY

12.1 Mechanism of Action

Caspofungin is an echinocandin antifungal drug [see Microbiology (12.4)].

12.3 Pharmacokinetics

Adult and pediatric pharmacokinetic parameters are presented in Table 8.

Distribution

Plasma concentrations of caspofungin decline in a polyphasic manner following single 1-hour IV infusions. A short α-phase occurs immediately postinfusion, followed by a β-phase (half-life of 9 to 11 hours) that characterizes much of the profile and exhibits clear log-linear behavior from 6 to 48 hours postdose during which the plasma concentration decreases 10-fold. An additional, longer half-life phase, γ-phase, (half-life of 40-50 hours), also occurs. Distribution, rather than excretion or biotransformation, is the dominant mechanism influencing plasma clearance. Caspofungin is extensively bound to albumin (~97%), and distribution into red blood cells is minimal. Mass balance results showed that approximately 92% of the administered radioactivity was distributed to tissues by 36 to 48 hours after a single 70-mg dose of [^3H] CANCIDAS. There is little excretion or biotransformation of caspofungin during the first 30 hours after administration.

Metabolism

Caspofungin is slowly metabolized by hydrolysis and N-acetylation. Caspofungin also undergoes spontaneous chemical degradation to an open-ring peptide compound, L-747969. At later time points (≥5 days postdose), there is a low level (≤7 picomoles/mg protein, or ≤1.3% of administered dose) of covalent binding of radiolabel in plasma following single-dose administration of [^3H] CANCIDAS, which may be due to two reactive intermediates formed during the chemical degradation of caspofungin to L-747969. Additional metabolism involves hydrolysis into constitutive amino acids and their degradates, including dihydroxyhomotyrosine and N-acetyl-dihydroxyhomotyrosine. These two tyrosine derivatives are found only in urine, suggesting rapid clearance of these derivatives by the kidneys.

Excretion

Two single-dose radiolabeled pharmacokinetic studies were conducted. In one study, plasma, urine, and feces were collected over 27 days, and in the second study plasma was collected over 6 months. Plasma concentrations of radioactivity and of caspofungin were similar during the first 24 to 48 hours postdose; thereafter drug levels fell more rapidly. In plasma, caspofungin concentrations fell below the limit of quantitation after 6 to 8 days postdose, while radiolabel fell below the limit of quantitation at 22.3 weeks postdose. After single intravenous administration of [^3H] CANCIDAS, excretion of caspofungin and its metabolites in humans was 35% of dose in feces and 41% of dose in urine. A small amount of caspofungin is excreted unchanged in urine (~1.4% of dose). Renal clearance of parent drug is low (~0.15 mL/min) and total clearance of caspofungin is 12 mL/min.

Special Populations

Renal Impairment

In a clinical study of single 70-mg doses, caspofungin pharmacokinetics were similar in healthy adult volunteers with mild renal impairment (creatinine clearance 50 to 80 mL/min) and control subjects. Moderate (creatinine clearance 31 to 49 mL/min), severe (creatinine clearance 5 to 30 mL/min), and end-stage (creatinine clearance less than 10 mL/min and dialysis dependent) renal impairment moderately increased caspofungin plasma concentrations after single-dose administration (range: 30 to 49% for AUC). However, in adult patients with invasive aspergillosis, candidemia, or other Candida infections (intra-abdominal abscesses, peritonitis, or pleural space infections) who received multiple daily doses of CANCIDAS 50 mg, there was no significant effect of mild to end-stage renal impairment on caspofungin concentrations. No dosage adjustment is necessary for patients with renal impairment. Caspofungin is not dialyzable, thus supplementary dosing is not required following hemodialysis.

Hepatic Impairment

Plasma concentrations of caspofungin after a single 70-mg dose in adult patients with mild hepatic impairment (Child-Pugh score 5 to 6) were increased by approximately 55% in AUC compared to healthy control subjects. In a 14-day multiple-dose study (70 mg on Day 1 followed by 50 mg daily thereafter), plasma concentrations in adult patients with mild hepatic impairment were increased modestly (19 to 25% in AUC) on Days 7 and 14 relative to healthy control subjects. No dosage adjustment is recommended for patients with mild hepatic impairment.

Adult patients with moderate hepatic impairment (Child-Pugh score 7 to 9) who received a single 70-mg dose of CANCIDAS had an average plasma caspofungin increase of 76% in AUC compared to control subjects. A dosage reduction is recommended for adult patients with moderate hepatic impairment based upon these pharmacokinetic data [see Dosage and Administration (2.4)].

There is no clinical experience in adult patients with severe hepatic impairment (Child-Pugh score greater than 9) or in pediatric patients with any degree of hepatic impairment.

Gender

Plasma concentrations of caspofungin in healthy adult men and women were similar following a single 70-mg dose. After 13 daily 50-mg doses, caspofungin plasma concentrations in women were elevated slightly (approximately 22% in area under the curve [AUC]) relative to men. No dosage adjustment is necessary based on gender.

Race

Regression analyses of patient pharmacokinetic data indicated that no clinically significant differences in the pharmacokinetics of caspofungin were seen among Caucasians, Blacks, and Hispanics. No dosage adjustment is necessary on the basis of race.

Geriatric Patients

Plasma concentrations of caspofungin in healthy older men and women (65 years of age and older) were increased slightly (approximately 28% AUC) compared to young healthy men after a single 70-mg dose of caspofungin. In patients who were treated empirically or who had candidemia or other Candida infections (intra-abdominal abscesses, peritonitis, or pleural space infections), a similar modest effect of age was seen in older patients relative to younger patients. No dosage adjustment is necessary for the elderly [see Use in Specific Populations (8.5)].

Pediatric Patients

CANCIDAS has been studied in five prospective studies involving pediatric patients under 18 years of age, including three pediatric pharmacokinetic studies [initial study in adolescents (12-17 years of age) and children (2-11 years of age) followed by a study in younger patients (3-23 months of age) and then followed by a study in neonates and infants (less than 3 months of age)] [see Use in Specific Populations (8.4)].

Pharmacokinetic parameters following multiple doses of CANCIDAS in pediatric and adult patients are presented in Table 8.

Table 8: Pharmacokinetic Parameters Following Multiple Doses of CANCIDAS in Pediatric (3 months to 17 years) and Adult Patients
Population | N | Daily Dose | Pharmacokinetic Parameters (Mean ± Standard Deviation)
Population | N | Daily Dose | AUC0-24hr (μg∙hr/mL) | C1hr (μg/mL) | C24hr (μg/mL) | t1/2 (hr) [Harmonic Mean ± jackknife standard deviation] | CI (mL/min)
PEDIATRIC PATIENTS
Adolescents, Aged 12-17 years | 8 | 50 mg/m^2 | 124.9 ± 50.4 | 14.0 ± 6.9 | 2.4 ± 1.0 | 11.2 ± 1.7 | 12.6 ± 5.5
Children, Aged 2-11 years | 9 | 50 mg/m^2 | 120.0 ± 33.4 | 16.1 ± 4.2 | 1.7 ± 0.8 | 8.2 ± 2.4 | 6.4 ± 2.6
Young Children, Aged 3-23 months | 8 | 50 mg/m^2 | 131.2 ± 17.7 | 17.6 ± 3.9 | 1.7 ± 0.7 | 8.8 ± 2.1 | 3.2 ± 0.4
ADULT PATIENTS
Adults with Esophageal Candidiasis | 6 [N=5 for C1hr and AUC0-24hr; N=6 for C24hr] | 50 mg | 87.3 ± 30.0 | 8.7 ± 2.1 | 1.7 ± 0.7 | 13.0 ± 1.9 | 10.6 ± 3.8
Adults receiving Empirical Therapy | 119 [N=117 for C24hr; N=119 for C1hr] | 50 mg [Following an initial 70-mg loading dose on day 1] | -- | 8.0 ± 3.4 | 1.6 ± 0.7 | -- | --

Drug Interactions [see Drug Interactions (7)]

Studies in vitro show that caspofungin acetate is not an inhibitor of any enzyme in the cytochrome P (CYP) system. Caspofungin is not a substrate for P-glycoprotein and is a poor substrate for CYP enzymes.

In clinical studies, caspofungin did not induce the CYP3A4 metabolism of other drugs. Clinical studies in adult healthy volunteers also demonstrated that the pharmacokinetics of caspofungin are not altered by itraconazole, amphotericin B, mycophenolate, nelfinavir, or tacrolimus. Caspofungin has no effect on the pharmacokinetics of itraconazole, amphotericin B, or the active metabolite of mycophenolate.

Cyclosporine: In two adult clinical studies, cyclosporine (one 4 mg/kg dose or two 3 mg/kg doses) increased the AUC of caspofungin by approximately 35%. CANCIDAS did not increase the plasma levels of cyclosporine. There were transient increases in liver ALT and AST when CANCIDAS and cyclosporine were co-administered [see Warnings and Precautions (5.2)].

Tacrolimus: CANCIDAS reduced the blood AUC0-12 of tacrolimus (FK-506, Prograf®) by approximately 20%, peak blood concentration (Cmax) by 16%, and 12-hour blood concentration (C12hr) by 26% in healthy adult subjects when tacrolimus (2 doses of 0.1 mg/kg 12 hours apart) was administered on the 10th day of CANCIDAS 70 mg daily, as compared to results from a control period in which tacrolimus was administered alone. For patients receiving both therapies, standard monitoring of tacrolimus whole blood trough concentrations and appropriate tacrolimus dosage adjustments are recommended.

Rifampin: A drug-drug interaction study with rifampin in adult healthy volunteers has shown a 30% decrease in caspofungin trough concentrations [see Dosage and Administration (2.5)].

Other Inducers of Hepatic CYP Enzymes

Adults: Results from regression analyses of adult patient pharmacokinetic data suggest that co-administration of other hepatic CYP enzyme inducers (e.g., efavirenz, nevirapine, phenytoin, dexamethasone, or carbamazepine) with CANCIDAS may result in clinically meaningful reductions in caspofungin concentrations. It is not known which drug clearance mechanism involved in caspofungin disposition may be inducible [see Dosage and Administration (2.5)].

Pediatric patients: In pediatric patients, results from regression analyses of pharmacokinetic data suggest that co-administration of dexamethasone with CANCIDAS may result in clinically meaningful reductions in caspofungin trough concentrations. This finding may indicate that pediatric patients will have similar reductions with inducers as seen in adults [see Dosage and Administration (2.5)].

12.4 Microbiology

Mechanism of Action

Caspofungin, an echinocandin, inhibits the synthesis of beta (1,3)-D-glucan, an essential component of the cell wall of susceptible Aspergillus species and Candida species. Beta (1,3)-D-glucan is not present in mammalian cells. Caspofungin has shown activity against Candida species and in regions of active cell growth of the hyphae of Aspergillus fumigatus.

Resistance

There have been reports of clinical failures in patients receiving caspofungin therapy due to the development of drug resistant Candida or Aspergillus species. Some of these reports have identified specific mutations in the Fks subunits, encoded by the fks1 and/or fks2 genes, of the glucan synthase enzyme. These mutations are associated with higher MICs and breakthrough infection. Candida species that exhibit reduced susceptibility to caspofungin as a result of an increase in the chitin content of the fungal cell wall have also been identified, although the significance of this phenomenon in vivo is not well known.

Interaction With Other Antimicrobials

Studies in vitro and in vivo of caspofungin, in combination with amphotericin B, suggest no antagonism of antifungal activity against either A. fumigatus or C. albicans. The clinical significance of these results is unknown.

Antimicrobial Activity

Caspofungin has been shown to be active against most strains of the following microorganisms both in vitro and in clinical infections [see Indications and Usage (1)]:

Aspergillus flavus
Aspergillus fumigatus
Aspergillus terreus
Candida albicans
Candida glabrata
Candida guilliermondii
Candida krusei
Candida parapsilosis
Candida tropicalis

Susceptibility Testing

For specific information regarding susceptibility test interpretive criteria and associated test methods and quality control standards recognized by FDA for caspofungin, please see: https://www.fda.gov/STIC.

13 NONCLINICAL TOXICOLOGY

13.1 Carcinogenesis, Mutagenesis, Impairment of Fertility

No long-term studies in animals have been performed to evaluate the carcinogenic potential of caspofungin.

Caspofungin did not show evidence of mutagenic or genotoxic potential when evaluated in the following in vitro assays: bacterial (Ames) and mammalian cell (V79 Chinese hamster lung fibroblasts) mutagenesis assays, the alkaline elution/rat hepatocyte DNA strand break test, and the chromosome aberration assay in Chinese hamster ovary cells. Caspofungin was not genotoxic when assessed in the mouse bone marrow chromosomal test at doses up to 12.5 mg/kg (equivalent to a human dose of 1 mg/kg based on body surface area comparisons), administered intravenously.

Fertility and reproductive performance were not affected by the intravenous administration of caspofungin to rats at doses up to 5 mg/kg. At 5 mg/kg exposures were similar to those seen in patients treated with the 70-mg dose.

13.2 Animal Toxicology and/or Pharmacology

In one 5-week study in monkeys at doses which produced exposures approximately 4 to 6 times those seen in adult patients treated with a 70-mg dose, scattered small foci of subcapsular necrosis were observed microscopically in the livers of some animals (2/8 monkeys at 5 mg/kg and 4/8 monkeys at 8 mg/kg); however, this histopathological finding was not seen in another study of 27 weeks duration at similar doses.

No treatment-related findings were seen in a 5-week study in infant monkeys at doses which produced exposures approximately 3 times those achieved in pediatric patients receiving a maintenance dose of 50 mg/m^2 daily.

14 CLINICAL STUDIES

14.1 Empirical Therapy in Febrile, Neutropenic Patients

A double-blind study enrolled 1111 febrile, neutropenic (<500 cells/mm^3) patients who were randomized to treatment with daily doses of CANCIDAS (50 mg/day following a 70-mg loading dose on Day 1) or AmBisome (3 mg/kg/day). Patients were stratified based on risk category (high-risk patients had undergone allogeneic stem cell transplantation or had relapsed acute leukemia) and on receipt of prior antifungal prophylaxis. Twenty-four percent of patients were high risk and 56% had received prior antifungal prophylaxis. Patients who remained febrile or clinically deteriorated following 5 days of therapy could receive 70 mg/day of CANCIDAS or 5 mg/kg/day of AmBisome. Treatment was continued to resolution of neutropenia (but not beyond 28 days unless a fungal infection was documented).

An overall favorable response required meeting each of the following criteria: no documented breakthrough fungal infections up to 7 days after completion of treatment, survival for 7 days after completion of study therapy, no discontinuation of the study drug because of drug-related toxicity or lack of efficacy, resolution of fever during the period of neutropenia, and successful treatment of any documented baseline fungal infection.

Based on the composite response rates, CANCIDAS was as effective as AmBisome in empirical therapy of persistent febrile neutropenia (see Table 9).

Table 9: Favorable Response of Patients with Persistent Fever and Neutropenia
 | CANCIDAS [CANCIDAS: 70 mg on Day 1, then 50 mg once daily for the remainder of treatment (daily dose increased to 70 mg for 73 patients); AmBisome: 3 mg/kg/day (daily dose increased to 5 mg/kg for 74 patients).] | AmBisome | % Difference (Confidence Interval) [Overall Response: estimated % difference adjusted for strata and expressed as CANCIDAS – AmBisome (95.2% CI); Individual criteria presented above are not mutually exclusive. The percent difference calculated as CANCIDAS – AmBisome.]
Number of Patients [Analysis population excluded subjects who did not have fever or neutropenia at study entry.] | 556 | 539
Overall Favorable Response | 190 (33.9%) | 181 (33.7%) | 0.2 (-5.6, 6.0)
No documented breakthrough fungal infection | 527 (94.8%) | 515 (95.5%) | -0.8
Survival 7 days after end of treatment | 515 (92.6%) | 481 (89.2%) | 3.4
No discontinuation due to toxicity or lack of efficacy | 499 (89.7%) | 461 (85.5%) | 4.2
Resolution of fever during neutropenia | 229 (41.2%) | 223 (41.4%) | -0.2

The rate of successful treatment of documented baseline infections, a component of the primary endpoint, was not statistically different between treatment groups.

The response rates did not differ between treatment groups based on either of the stratification variables: risk category or prior antifungal prophylaxis.

14.2 Candidemia and the Following other Candida Infections: Intra-Abdominal Abscesses, Peritonitis and Pleural Space Infections

In a randomized, double-blind study, patients with a proven diagnosis of invasive candidiasis received daily doses of CANCIDAS (50 mg/day following a 70-mg loading dose on Day 1) or amphotericin B deoxycholate (0.6 to 0.7 mg/kg/day for non-neutropenic patients and 0.7 to 1 mg/kg/day for neutropenic patients). Patients were stratified by both neutropenic status and APACHE II score. Patients with Candida endocarditis, meningitis, or osteomyelitis were excluded from this study.

Patients who met the entry criteria and received one or more doses of IV study therapy were included in the modified intention-to-treat [MITT] analysis of response at the end of IV study therapy. A favorable response at this time point required both symptom/sign resolution/improvement and microbiological clearance of the Candida infection.

Two hundred thirty-nine patients were enrolled. Patient disposition is shown in Table 10.

Table 10: Disposition in Candidemia and Other Candida Infections (Intra-abdominal abscesses, peritonitis, and pleural space infections)
 | CANCIDAS [Patients received CANCIDAS 70 mg on Day 1, then 50 mg once daily for the remainder of their treatment.] | Amphotericin B
Randomized patients | 114 | 125
Patients completing study [Study defined as study treatment period and 6-8 week follow-up period.] | 63 (55.3%) | 69 (55.2%)
DISCONTINUATIONS OF STUDY
All Study Discontinuations | 51 (44.7%) | 56 (44.8%)
Study Discontinuations due to clinical adverse events | 39 (34.2%) | 43 (34.4%)
Study Discontinuations due to laboratory adverse events | 0 (0%) | 1 (0.8%)
DISCONTINUATIONS OF STUDY THERAPY
All Study Therapy Discontinuations | 48 (42.1%) | 58 (46.4%)
Study Therapy Discontinuations due to clinical adverse events | 30 (26.3%) | 37 (29.6%)
Study Therapy Discontinuations due to laboratory adverse events | 1 (0.9%) | 7 (5.6%)
Study Therapy Discontinuations due to all drug-related [Determined by the investigator to be possibly, probably, or definitely drug-related.] adverse events | 3 (2.6%) | 29 (23.2%)

Of the 239 patients enrolled, 224 met the criteria for inclusion in the MITT population (109 treated with CANCIDAS and 115 treated with amphotericin B). Of these 224 patients, 186 patients had candidemia (92 treated with CANCIDAS and 94 treated with amphotericin B). The majority of the patients with candidemia were non-neutropenic (87%) and had an APACHE II score less than or equal to 20 (77%) in both arms. Most candidemia infections were caused by C. albicans (39%), followed by C. parapsilosis (20%), C. tropicalis (17%), C. glabrata (8%), and C. krusei (3%).

At the end of IV study therapy, CANCIDAS was comparable to amphotericin B in the treatment of candidemia in the MITT population. For the other efficacy time points (Day 10 of IV study therapy, end of all antifungal therapy, 2-week post-therapy follow-up, and 6- to 8-week post-therapy follow-up), CANCIDAS was as effective as amphotericin B.

Outcome, relapse and mortality data are shown in Table 11.

Table 11: Outcomes, Relapse, & Mortality in Candidemia and Other Candida Infections (Intra-abdominal abscesses, peritonitis, and pleural space infections)
 | CANCIDAS [Patients received CANCIDAS 70 mg on Day 1, then 50 mg once daily for the remainder of their treatment.] | Amphotericin B | % Difference [Calculated as CANCIDAS – amphotericin B] after adjusting for strata (Confidence Interval) [95% CI for candidemia, 95.6% for all patients]
Number of MITT [Modified intention-to-treat] patients | 109 | 115
FAVORABLE OUTCOMES (MITT) AT THE END OF IV STUDY THERAPY
All MITT patients | 81/109 (74.3%) | 78/115 (67.8%) | 7.5 (-5.4, 20.3)
Candidemia | 67/92 (72.8%) | 63/94 (67.0%) | 7.0 (-7.0, 21.1)
Neutropenic | 6/14 (43%) | 5/10 (50%)
Non-neutropenic | 61/78 (78%) | 58/84 (69%)
Endophthalmitis | 0/1 | 2/3
Multiple Sites | 4/5 | 4/4
Blood / Pleural | 1/1 | 1/1
Blood / Peritoneal | 1/1 | 1/1
Blood / Urine | - | 1/1
Peritoneal / Pleural | 1/2 | -
Abdominal / Peritoneal | - | 1/1
Subphrenic / Peritoneal | 1/1 | -
DISSEMINATED INFECTIONS, RELAPSES AND MORTALITY
Disseminated Infections in neutropenic patients | 4/14 (28.6%) | 3/10 (30.0%)
All relapses [Includes all patients who either developed a culture-confirmed recurrence of Candida infection or required antifungal therapy for the treatment of a proven or suspected Candida infection in the follow-up period.] | 7/81 (8.6%) | 8/78 (10.3%)
Culture-confirmed relapse | 5/81 (6%) | 2/78 (3%)
Overall study [Study defined as study treatment period and 6-8 week follow-up period.] mortality in MITT | 36/109 (33.0%) | 35/115 (30.4%)
Mortality during study therapy | 18/109 (17%) | 13/115 (11%)
Mortality attributed to Candida | 4/109 (4%) | 7/115 (6%)

In this study, the efficacy of CANCIDAS in patients with intra-abdominal abscesses, peritonitis and pleural space Candida infections was evaluated in 19 non-neutropenic patients. Two of these patients had concurrent candidemia. Candida was part of a polymicrobial infection that required adjunctive surgical drainage in 11 of these 19 patients. A favorable response was seen in 9 of 9 patients with peritonitis, 3 of 4 with abscesses (liver, parasplenic, and urinary bladder abscesses), 2 of 2 with pleural space infections, 1 of 2 with mixed peritoneal and pleural infection, 1 of 1 with mixed abdominal abscess and peritonitis, and 0 of 1 with Candida pneumonia.

Overall, across all sites of infection included in the study, the efficacy of CANCIDAS was comparable to that of amphotericin B for the primary endpoint.

In this study, the efficacy data for CANCIDAS in neutropenic patients with candidemia were limited. In a separate compassionate use study, 4 patients with hepatosplenic candidiasis received prolonged therapy with CANCIDAS following other long-term antifungal therapy; three of these patients had a favorable response.

In a second randomized, double-blind study, 197 patients with proven invasive candidiasis received CANCIDAS 50 mg/day (following a 70-mg loading dose on Day 1) or CANCIDAS 150 mg/day. The diagnostic criteria, evaluation time points, and efficacy endpoints were similar to those employed in the prior study. Patients with Candida endocarditis, meningitis, or osteomyelitis were excluded. Although this study was designed to compare the safety of the two doses, it was not large enough to detect differences in rare or unexpected adverse events [see Adverse Reactions (6.1)]. The efficacy of CANCIDAS at the 150 mg daily dose was not significantly better than the efficacy of the 50-mg daily dose of CANCIDAS. The efficacy of doses higher than 50 mg daily in the other adult patients for whom CANCIDAS is indicated has not been evaluated.

14.3 Esophageal Candidiasis (and information on oropharyngeal candidiasis)

The safety and efficacy of CANCIDAS in the treatment of esophageal candidiasis was evaluated in one large, controlled, noninferiority, clinical trial and two smaller dose-response studies.

In all 3 studies, patients were required to have symptoms and microbiological documentation of esophageal candidiasis; most patients had advanced AIDS (with CD4 counts <50/mm^3).

Of the 166 patients in the large study who had culture-confirmed esophageal candidiasis at baseline, 120 had Candida albicans and 2 had Candida tropicalis as the sole baseline pathogen whereas 44 had mixed baseline cultures containing C. albicans and one or more additional Candida species.

In the large, randomized, double-blind study comparing CANCIDAS 50 mg/day versus intravenous fluconazole 200 mg/day for the treatment of esophageal candidiasis, patients were treated for an average of 9 days (range 7-21 days). Favorable overall response at 5 to 7 days following discontinuation of study therapy required both complete resolution of symptoms and significant endoscopic improvement. The definition of endoscopic response was based on severity of disease at baseline using a 4-grade scale and required at least a two-grade reduction from baseline endoscopic score or reduction to grade 0 for patients with a baseline score of 2 or less.

The proportion of patients with a favorable overall response was comparable for CANCIDAS and fluconazole as shown in Table 12.

Table 12: Favorable Response Rates for Patients with Esophageal Candidiasis [Analysis excluded patients without documented esophageal candidiasis or patients not receiving at least 1 day of study therapy.]
 | CANCIDAS | Fluconazole | % Difference [Calculated as CANCIDAS – fluconazole] (95% CI)
Day 5-7 post-treatment | 66/81 (81.5%) | 80/94 (85.1%) | -3.6 (-14.7, 7.5)

The proportion of patients with a favorable symptom response was also comparable (90.1% and 89.4% for CANCIDAS and fluconazole, respectively). In addition, the proportion of patients with a favorable endoscopic response was comparable (85.2% and 86.2% for CANCIDAS and fluconazole, respectively).

As shown in Table 13, the esophageal candidiasis relapse rates at the Day 14 post-treatment visit were similar for the two groups. At the Day 28 post-treatment visit, the group treated with CANCIDAS had a numerically higher incidence of relapse; however, the difference was not statistically significant.

Table 13: Relapse Rates at 14 and 28 Days Post-Therapy in Patients with Esophageal Candidiasis at Baseline
 | CANCIDAS | Fluconazole | % Difference [Calculated as CANCIDAS – fluconazole] (95% CI)
Day 14 post-treatment | 7/66 (10.6%) | 6/76 (7.9%) | 2.7 (-6.9, 12.3)
Day 28 post-treatment | 18/64 (28.1%) | 12/72 (16.7%) | 11.5 (-2.5, 25.4)

In this trial, which was designed to establish noninferiority of CANCIDAS to fluconazole for the treatment of esophageal candidiasis, 122 (70%) patients also had oropharyngeal candidiasis. A favorable response was defined as complete resolution of all symptoms of oropharyngeal disease and all visible oropharyngeal lesions. The proportion of patients with a favorable oropharyngeal response at the 5- to 7-day post-treatment visit was numerically lower for CANCIDAS; however, the difference was not statistically significant. Oropharyngeal candidiasis relapse rates at Day 14 and Day 28 post-treatment visits were statistically significantly higher for CANCIDAS than for fluconazole. The results are shown in Table 14.

Table 14: Oropharyngeal Candidiasis Response Rates at 5 to 7 Days Post-Therapy and Relapse Rates at 14 and 28 Days Post-Therapy in Patients with Oropharyngeal and Esophageal Candidiasis at Baseline
 | CANCIDAS | Fluconazole | % Difference [Calculated as CANCIDAS – fluconazole] (95% CI)
Response Rate Day 5-7 post-treatment | 40/56 (71.4%) | 55/66 (83.3%) | -11.9 (-26.8, 3.0)
Relapse Rate Day 14 post-treatment | 17/40 (42.5%) | 7/53 (13.2%) | 29.3 (11.5, 47.1)
Relapse Rate Day 28 post-treatment | 23/39 (59.0%) | 18/51 (35.3%) | 23.7 (3.4, 43.9)

The results from the two smaller dose-ranging studies corroborate the efficacy of CANCIDAS for esophageal candidiasis that was demonstrated in the larger study.

CANCIDAS was associated with favorable outcomes in 7 of 10 esophageal C. albicans infections refractory to at least 200 mg of fluconazole given for 7 days, although the in vitro susceptibility of the infecting isolates to fluconazole was not known.

14.4 Invasive Aspergillosis

Sixty-nine patients between the ages of 18 and 80 with invasive aspergillosis were enrolled in an open-label, noncomparative study to evaluate the safety, tolerability, and efficacy of CANCIDAS. Enrolled patients had previously been refractory to or intolerant of other antifungal therapy(ies). Refractory patients were classified as those who had disease progression or failed to improve despite therapy for at least 7 days with amphotericin B, lipid formulations of amphotericin B, itraconazole, or an investigational azole with reported activity against Aspergillus. Intolerance to previous therapy was defined as a doubling of creatinine (or creatinine ≥2.5 mg/dL while on therapy), other acute reactions, or infusion-related toxicity. To be included in the study, patients with pulmonary disease must have had definite (positive tissue histopathology or positive culture from tissue obtained by an invasive procedure) or probable (positive radiographic or computed tomography evidence with supporting culture from bronchoalveolar lavage or sputum, galactomannan enzyme-linked immunosorbent assay, and/or polymerase chain reaction) invasive aspergillosis. Patients with extrapulmonary disease had to have definite invasive aspergillosis. Patients were administered a single 70-mg loading dose of CANCIDAS and subsequently dosed with 50 mg daily. The mean duration of therapy was 33.7 days, with a range of 1 to 162 days.

An independent expert panel evaluated patient data, including diagnosis of invasive aspergillosis, response and tolerability to previous antifungal therapy, treatment course on CANCIDAS, and clinical outcome.

A favorable response was defined as either complete resolution (complete response) or clinically meaningful improvement (partial response) of all signs and symptoms and attributable radiographic findings. Stable, nonprogressive disease was considered to be an unfavorable response.

Among the 69 patients enrolled in the study, 63 met entry diagnostic criteria and had outcome data; and of these, 52 patients received treatment for greater than 7 days. Fifty-three (84%) were refractory to previous antifungal therapy and 10 (16%) were intolerant. Forty-five patients had pulmonary disease and 18 had extrapulmonary disease. Underlying conditions were hematologic malignancy (N=24), allogeneic bone marrow transplant or stem cell transplant (N=18), organ transplant (N=8), solid tumor (N=3), or other conditions (N=10). All patients in the study received concomitant therapies for their other underlying conditions. Eighteen patients received tacrolimus and CANCIDAS concomitantly, of whom 8 also received mycophenolate mofetil.

Overall, the expert panel determined that 41% (26/63) of patients receiving at least one dose of CANCIDAS had a favorable response. For those patients who received greater than 7 days of therapy with CANCIDAS, 50% (26/52) had a favorable response. The favorable response rates for patients who were either refractory to or intolerant of previous therapies were 36% (19/53) and 70% (7/10), respectively. The response rates among patients with pulmonary disease and extrapulmonary disease were 47% (21/45) and 28% (5/18), respectively. Among patients with extrapulmonary disease, 2 of 8 patients who also had definite, probable, or possible CNS involvement had a favorable response. Two of these 8 patients had progression of disease and manifested CNS involvement while on therapy.

CANCIDAS is effective for the treatment of invasive aspergillosis in patients who are refractory to or intolerant of itraconazole, amphotericin B, and/or lipid formulations of amphotericin B. However, the efficacy of CANCIDAS for initial treatment of invasive aspergillosis has not been evaluated in comparator-controlled clinical studies.

14.5 Pediatric Patients

The safety and efficacy of CANCIDAS were evaluated in pediatric patients 3 months to 17 years of age in two prospective, multicenter clinical trials.

The first study, which enrolled 82 patients between 2 to 17 years of age, was a randomized, double-blind study comparing CANCIDAS (50 mg/m^2 IV once daily following a 70-mg/m^2 loading dose on Day 1 [not to exceed 70 mg daily]) to AmBisome (3 mg/kg IV daily) in a 2:1 treatment fashion (56 on caspofungin, 26 on AmBisome) as empirical therapy in pediatric patients with persistent fever and neutropenia. The study design and criteria for efficacy assessment were similar to the study in adult patients [see Clinical Studies (14.1)]. Patients were stratified based on risk category (high-risk patients had undergone allogeneic stem cell transplantation or had relapsed acute leukemia). Twenty-seven percent of patients in both treatment groups were high risk. Favorable overall response rates of pediatric patients with persistent fever and neutropenia are presented in Table 15.

Table 15: Favorable Overall Response Rates of Pediatric Patients with Persistent Fever and Neutropenia
 | CANCIDAS | AmBisome [One patient excluded from analysis due to no fever at study entry.]
Number of Patients | 56 | 25
Overall Favorable Response | 26/56 (46.4%) | 8/25 (32.0%)
High risk | 9/15 (60.0%) | 0/7 (0.0%)
Low risk | 17/41 (41.5%) | 8/18 (44.4%)

The second study was a prospective, open-label, non-comparative study estimating the safety and efficacy of caspofungin in pediatric patients (ages 3 months to 17 years) with candidemia and other Candida infections, esophageal candidiasis, and invasive aspergillosis (as salvage therapy). The study employed diagnostic criteria which were based on established EORTC/MSG criteria of proven or probable infection; these criteria were similar to those criteria employed in the adult studies for these various indications. Similarly, the efficacy time points and endpoints used in this study were similar to those employed in the corresponding adult studies [see Clinical Studies (14.2, 14.3, and 14.4)]. All patients received CANCIDAS at 50 mg/m^2 IV once daily following a 70-mg/m^2 loading dose on Day 1 (not to exceed 70 mg daily). Among the 49 enrolled patients who received CANCIDAS, 48 were included in the efficacy analysis (one patient excluded due to not having a baseline Aspergillus or Candida infection). Of these 48 patients, 37 had candidemia or other Candida infections, 10 had invasive aspergillosis, and 1 patient had esophageal candidiasis. Most candidemia and other Candida infections were caused by C. albicans (35%), followed by C. parapsilosis (22%), C. tropicalis (14%), and C. glabrata (11%). The favorable response rate, by indication, at the end of caspofungin therapy was as follows: 30/37 (81%) in candidemia or other Candida infections, 5/10 (50%) in invasive aspergillosis, and 1/1 in esophageal candidiasis.

15 REFERENCES

1. Mosteller RD: Simplified Calculation of Body Surface Area. N Engl J Med 1987 Oct 22;317(17): 1098 (letter).

16 HOW SUPPLIED/STORAGE AND HANDLING

How Supplied

CANCIDAS 50 mg is a lyophilized white to off-white cake or powder for intravenous infusion supplied in single-dose vials with a red aluminum band and a plastic cap.

NDC 0006-3822-10 supplied as one single-dose vial.

CANCIDAS 70 mg is a white to off-white powder/cake for infusion in a vial with a yellow/orange aluminum band and a plastic cap.

NDC 0006-3823-10 supplied as one single-dose vial.

Storage and Handling

The lyophilized vials should be stored refrigerated at 2° to 8°C (36° to 46°F).

17 PATIENT COUNSELING INFORMATION

Hypersensitivity

Inform patients that anaphylactic reactions have been reported during administration of CANCIDAS. CANCIDAS can cause hypersensitivity reactions, including rash, facial swelling, angioedema, pruritus, sensation of warmth, or bronchospasm. Inform patients to report these signs or symptoms to their healthcare providers.

Hepatic Effects

Inform patients that there have been isolated reports of serious hepatic effects from CANCIDAS therapy.

Use in Pregnancy and Breastfeeding Mothers

Advise female patients of the potential risks to a fetus. Instruct patients to tell their healthcare provider if they are pregnant, become pregnant, or are thinking about becoming pregnant. Instruct patients to tell their healthcare provider if they plan to breastfeed their infant.

Distributed by: Merck Sharp & Dohme LLC
Rahway, NJ 07065, USA

The trademarks depicted herein are owned by their respective companies.

Copyright © 2001-2022 Merck & Co., Inc., Rahway, NJ, USA, and its affiliates.

All rights reserved.

uspi-mk0991-i-2205r015

PRINCIPAL DISPLAY PANEL - 50 mg Vial Carton

NDC 0006-3822-10

Cancidas®
(caspofungin acetate)
For Injection

50 mg*

FOR INTRAVENOUS USE ONLY

*Vial contains 50 mg caspofungin
equivalent to 55.5 mg caspofungin
acetate. Reconstitute with 10.8 mL
of diluent to obtain a concentration
of 5 mg/mL.
Discard unused portion.
Requires further dilution prior
to infusion.

DO NOT USE DILUENTS
CONTAINING DEXTROSE
(α-D-glucose)

Single-Dose Vial
Rx only

PRINCIPAL DISPLAY PANEL - 70 mg Vial Carton

NDC 0006-3823-10

Cancidas®
(caspofungin acetate)
For Injection

70 mg*

FOR INTRAVENOUS USE ONLY

*Vial contains 70 mg caspofungin
equivalent to 77.7 mg caspofungin
acetate. Reconstitute with 10.8 mL
of diluent to obtain a concentration
of 7 mg/mL.
Discard unused portion.
Requires further dilution prior
to infusion.

DO NOT USE DILUENTS
CONTAINING DEXTROSE
(α-D-glucose)

Single-Dose Vial
Rx only